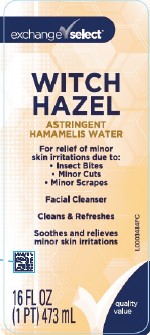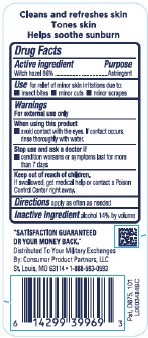 DRUG LABEL: Witch Hazel
NDC: 55301-822 | Form: LIQUID
Manufacturer: Your Military Exchanges
Category: otc | Type: HUMAN OTC DRUG LABEL
Date: 20260212

ACTIVE INGREDIENTS: WITCH HAZEL 860 mg/1 mL
INACTIVE INGREDIENTS: ALCOHOL

Exchange Select 822.001/822AA
Witch Hazel

Claims

Cleans and refreshes skin

Tones skin

Helps soothe sunburn

Active ingredient

Witch hazel 86%

purpose

Astringent

use

for relief of minor skin irritation due to:

- insect bites
- minor cuts
- minor scrapes

Warnings

For external use only

When using this product

• avoid contact with the eyes. If contact occurs, rinse thoroughly with water.

Stop use and ask a doctor if

•condition worsens or symptoms persist for more than 7 days

Keep out of reach of children.

If swallowed, get medical help or contact a Poison Control Center right away.

Directions

apply as often as needed

Inactive ingredient

alcohol 14% by volume

ADVERSE REACTION

"SATISFACTION GUARANTEED OR YOUR MONEY BACK"

Distributed To Your Military Exchange

By: Consumer Product Partners, LLC

St. Louis, MO 63114 • 1-888-593-0593

Pat. D675, 101

principal display panel

exchange select™

WITCH HAZEL

ASTRINGENT

HAMAMELIS WATER

For relief of minor skin irritations due to:

- Insect Bites
- Minor Cuts
- Minor Scrapes

Facial Cleanser

Cleans & Refreshes

Soothes and relieves minor skin irritations

quality value

16 FL OZ (1 PT) 473 mL